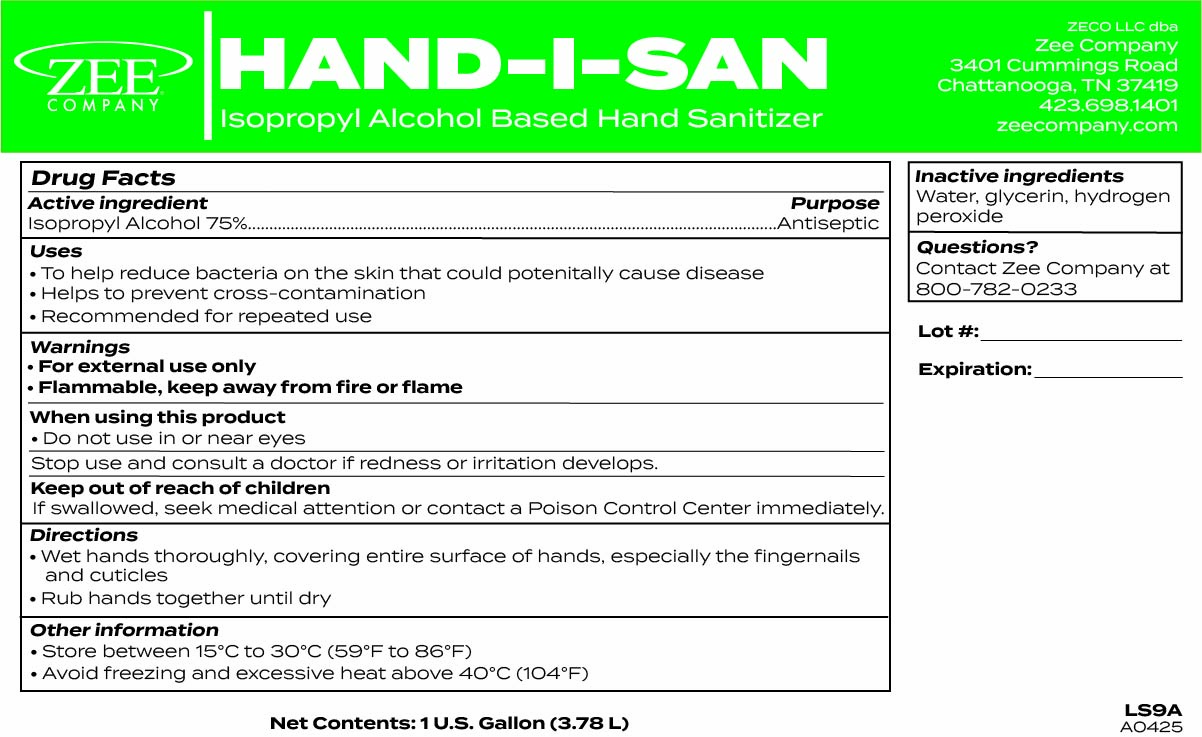 DRUG LABEL: HAND-I-SAN
NDC: 85820-900 | Form: LIQUID
Manufacturer: ZECO, LLC
Category: otc | Type: HUMAN OTC DRUG LABEL
Date: 20250613

ACTIVE INGREDIENTS: ISOPROPYL ALCOHOL 0.75 L/1 L
INACTIVE INGREDIENTS: GLYCERIN; HYDROGEN PEROXIDE; WATER

HAND-I-SAN

ACTIVE INGREDIENT

Isopropyl Alcohol 75%

Purpose

Hand Sanitizer

Uses

- To help reduce bacteria on the skin that could potenitally cause disease
- Helps to prevent cross-contamination
- Recommended for repeated use

Warnings

- For external use only
- Flammable, keep away from fire or flame

When using this product

- Do not use in or near eyes

Stop use and consult a doctor if redness or irritation develops.

Keep out of reach of children

If swallowed, seek medical attention or contact a Poison Control Center immediately.

Directions

- Wet hands thoroughly, covering entire surface of hands, especially the fingernails and cuticles
- Rub hands thoroughly until dry

Other information

- Store between 15°C to 30°C (59°F to 86°F)
- Avoid freezing and excessive heat above 40°C (104°F)

Inactive ingredients

Water, glycerin, hydrogen peroxide

Questions?

Contact Zee Company at 800-782-0233